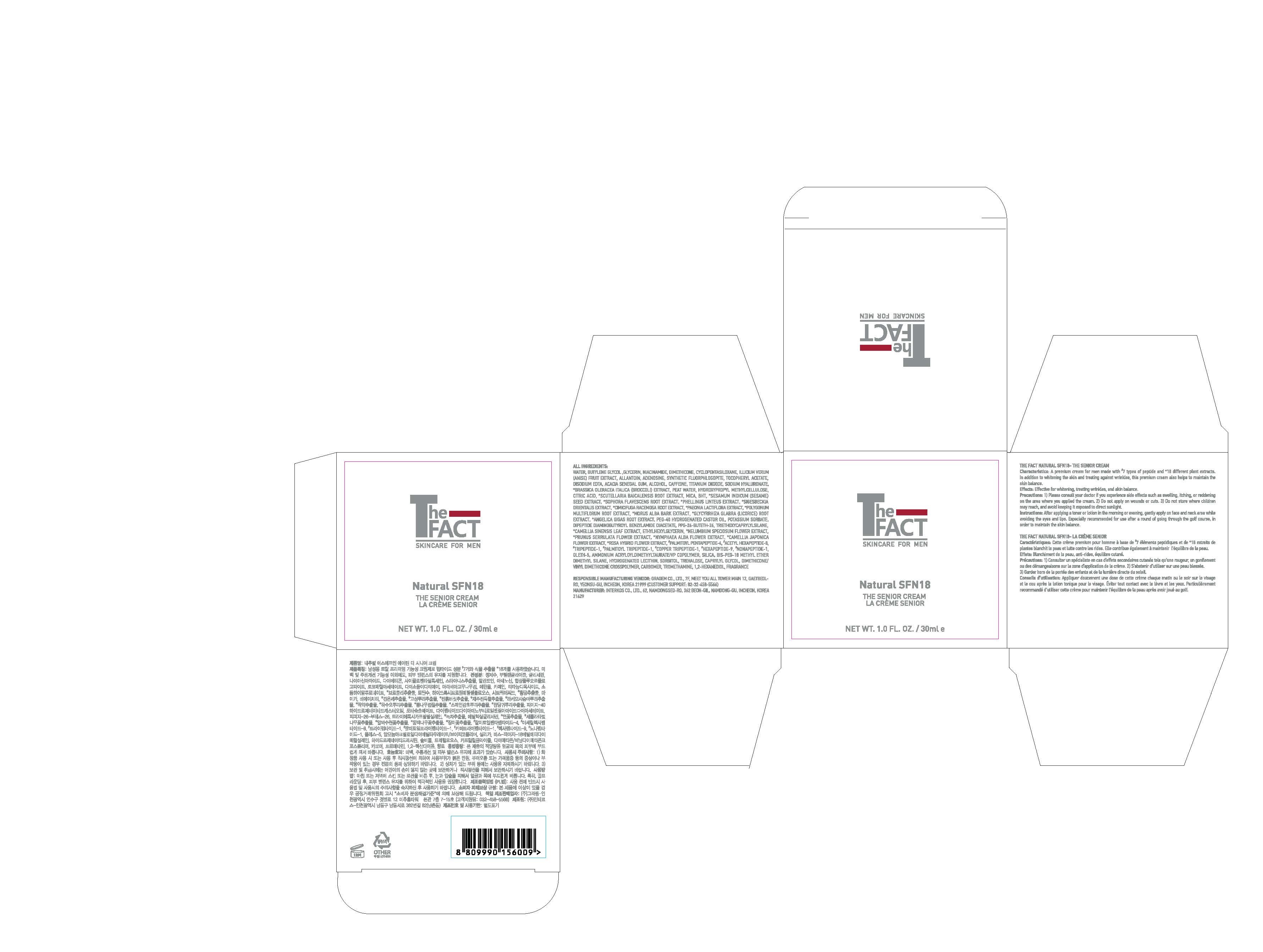 DRUG LABEL: The Fact Natural SPN18 - The SeniorCream
NDC: 77049-0001 | Form: CREAM
Manufacturer: Interkos Co.,Ltd.
Category: otc | Type: HUMAN OTC DRUG LABEL
Date: 20200502

ACTIVE INGREDIENTS: NIACINAMIDE 3 g/100 mL; ADENOSINE 0.04 g/100 mL
INACTIVE INGREDIENTS: BUTYLENE GLYCOL; GLYCERIN

Drug Facts

ACTIVE INGREDIENT

niacinamide, adenosine

INACTIVE INGREDIENT

water, butylene glycol, glycerin, dimethicone, cyclopentasiloxane, illicium verum(anise) fruit extract, allantoin, synthetic fluorphlogopite, tocopheryl acetate, disodium edta, acacia senegal gum, alcohol, cafeine, titanium dioxide, sodium hyaluronate, brassica oleracea italica (broccoli) extract, peat water, hydroxypropyl methylcellulose, citric acid, scutellaria baicalensis root extract, mica, BHT, sesamum indicum(sesame) seed extract, sophora flavescens root extract, phellinus linteus extract, sigesbeckia orientalis extract, cimicifuga racemosa root extract, paeonia lactiflora extract, polygonum multiflorum root extract, morus alba bark extract, glycyrrhiza glabra(licorice) root extract, angelica gigas root extract, PEG-40 hydrogenated castor oil, potassium sorbate, dipeptide diaminobutryroyl benzylamide diacetate, PPG-26-Buteth-26, triethoxycaprylylsilane, camellia sinensis leaf extract, ethylhexylglycerin, nelumbium speciosum flower extract, prunus serrulata flower extract, nymphaea alba flower extract, camellia japonica flower extract, rosa hybrid flower extract, palmitoyl pntapeptide-4, acetyl hexapeptide-8, tripeptide-1, palmitoyl tripeptide-1, copper tripeptide-1, hexapeptide-9, nonapeptide-1, oleth-5, ammonium acryloyldimethytaurate/vp copolymer, silica, BIS-PEG-18 methyl ether dimethyl silane, hydrogenated lecithin, sorbitol, trehalose, caprylrl glycol, dimethicone/vinyl dimethicone crosspolymer, carbomer, tromethamine, 1,2-hexanediol, fragrance

PURPOSE

for skin protectant

KEEP OUT OF REACH OF THE CHILDREN

INDICATIONS AND USAGE

After applying a toner or lotion in the morning or evening, gently apply on face and neck area while avoiding the eyes and lips. Especially recommended for use after a round of going through the golf course, in order to maintain the skin balance.

WARNINGS

1) Please consult your doctor if you experience side effects such as swelling, itching, or reddening on the area where you applied the cream.

2) Do not apply on wounds or cuts. 3) Do not store where children may reach, and avoid keeping it exposed to direct sunlight.

DOSAGE AND ADMINISTRATION

external use only